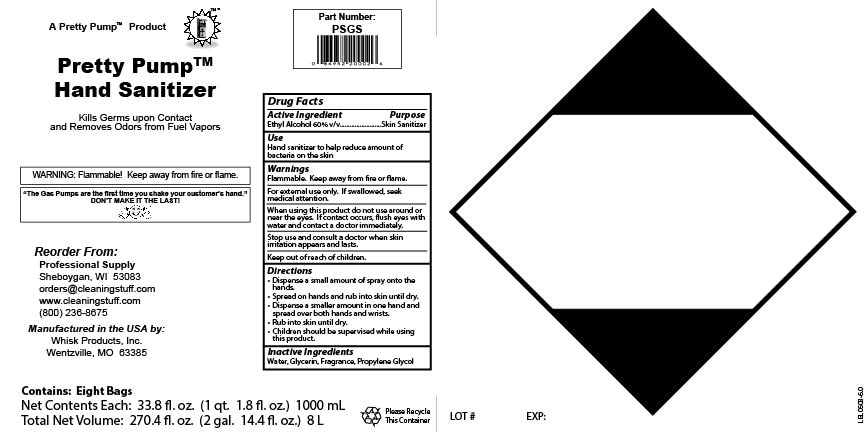 DRUG LABEL: Pretty Pump Hand Sanitizer
NDC: 65585-489 | Form: SPRAY
Manufacturer: Whisk Products, Inc.
Category: otc | Type: HUMAN OTC DRUG LABEL
Date: 20231208

ACTIVE INGREDIENTS: ALCOHOL 600 mL/1 L
INACTIVE INGREDIENTS: PROPYLENE GLYCOL; GLYCERIN; WATER

Pretty Pump Hand Sanitizer

Active Ingredient

Ethyl Alcohol 60% v/v

Purpose

Skin Sanitizer

Use

Hand sanitizer to help reduce amount of bacteria on the skin

Warnings

Flammable. Keep away from fire or flame.

For external use only. If swallowed, seek medical attention.

When using this product do not use around or near the eyes. If contact occurs, flush eyes with water and contact a doctor immediately.

Stop use and consult a doctor when skin irritation appears and lasts.

Keep out of reach of children.

Directions

- Dispense a small amount of spray onto the hands.
- Spread on hands and rub into skin until dry.
- Dispense a smaller amount in one hand and spread over both hands and wrists.
- Rub into skin until dry.
- Children should be supervised while using this product.

Inactive Ingredients

Water, Glycerin, Fragrance, Propylene Glycol